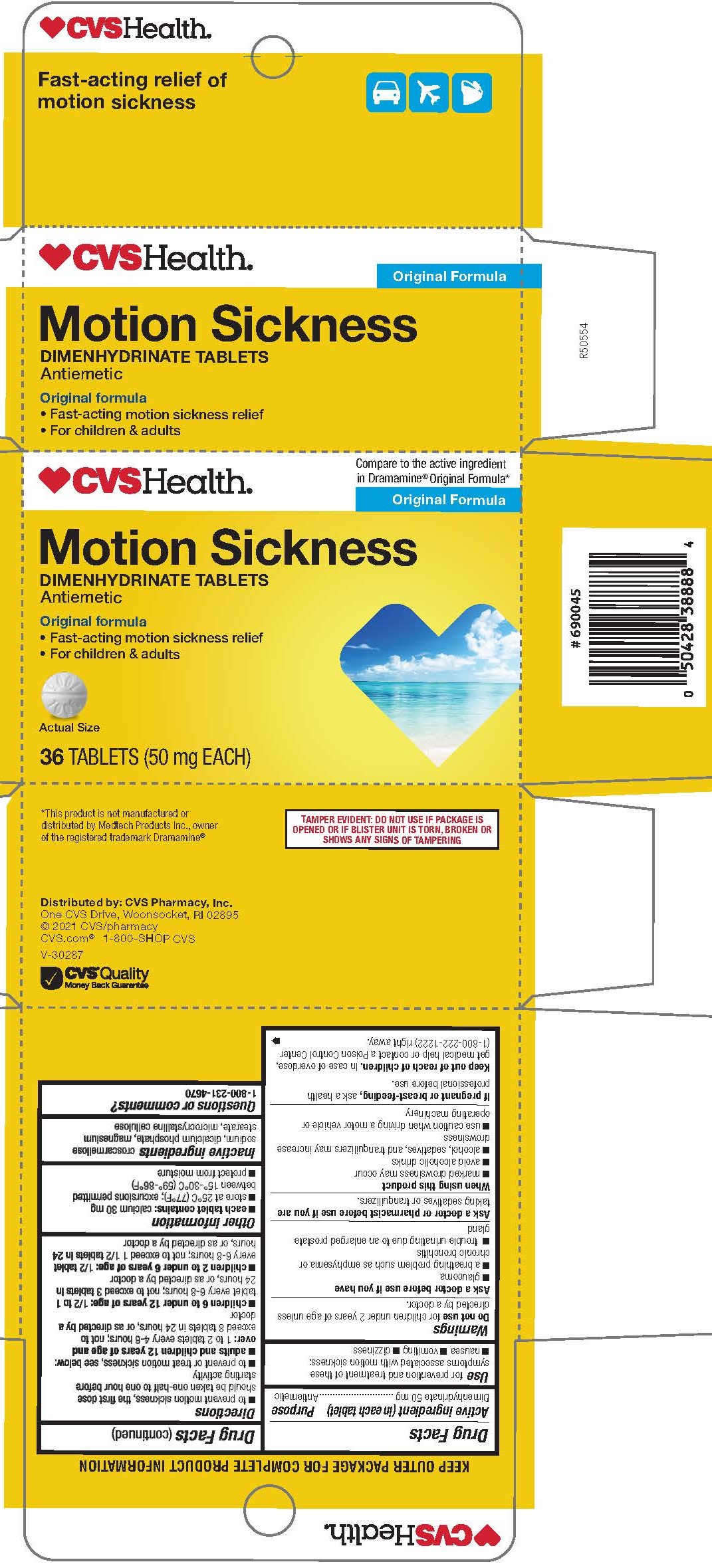 DRUG LABEL: Dimenhydrinate
NDC: 69842-206 | Form: TABLET
Manufacturer: CVS Pharmacy, Inc.
Category: otc | Type: HUMAN OTC DRUG LABEL
Date: 20241202

ACTIVE INGREDIENTS: DIMENHYDRINATE 50 mg/1 1
INACTIVE INGREDIENTS: MICROCRYSTALLINE CELLULOSE; CROSCARMELLOSE SODIUM; CALCIUM PHOSPHATE, DIBASIC, DIHYDRATE; MAGNESIUM STEARATE

1006-CVS

Drug Facts

Active ingredient (in each tablet)

Dimenhydrinate 50 mg

PURPOSE

Antiemetic

Uses

for the prevention and treatment of nausea, vomiting, or dizziness associated with motion sickness

WARNINGS

Do not use for children under 2 years of age unless directed by a doctor.

Ask a doctor before use if you have

- glaucoma
- a breathing problem such as emphysema or chronic bronchitis
- difficulty in urination due to an enlargement of the prostate gland

Ask a doctor or pharmacist before use if you are taking sedatives or tranquilizers.

When using this product

- marked drowsiness may occur
- avoid alcoholic drinks
- alcohol, sedatives, and tranquilizers may increase drowsiness
- use caution when driving a motor vehicle or operating machinery

PREGNANCY OR BREAST FEEDING

If pregnant or breast-feeding, ask a health professional before use.

Keep out of reach of children.

OVERDOSAGE

In case of overdose, get medical help or contact a Poison Control Center (1-800-222-1222) right away.

Directions

■ to prevent motion sickness, the first dose should be taken one-half to one hour before starting activity

■ adults and children 12 years of age and over: 1 to 2 tablets every 4-6 hours; not to exceed 8 tablets in 24 hours, or as directed by a doctor

■ children 6 to under 12 years of age: 1/2 to 1 tablet every 6-8 hours; not to exceed 3 tablets in 24 hours, or as directed by a doctor

■ children 2 to under 6 years of age: 1/2 tablet every 6-8 hours; not to exceed 1 1/2 tablets in 24 hours, or as directed by a doctor

Other Informations

■ each tablet contains: calcium 30 mg

■ store at 25°C (77°F); excursions permitted between 15°-30°C (59°-86°F)

■ protect from moisture

INACTIVE INGREDIENT

croscarmellose sodium, dicalcium phosphate, magnesium stearate, microcrystalline cellulose

Questions or comments?

1-800-231-4670

KEEP OUTER PACKAGE FOR COMPLETE PRODUCT INFORMATION

TAMPER EVIDENT: DO NOT USE IF PACKAGE IS OPENED OR IF BLISTER UNIT IS TORN, BROKEN OR SHOWS ANY SIGNS OF TAMPERING

* This product is not manufactured or distributed by Medtech Products Inc., owner of the registered trademark Dramamine®

Distributed by: CVS Pharmacy, Inc.

One CVS Drive, Woonsocket, RI 02895

© 2021 CVS/pha rmacy

CVS.com® 1-800-SHOP CVS

V-30287

PACKAGE LABEL

CVSHealth

Compare to the active ingredient in Dramamine® Original Formula*

Motion Sickness

DIMENHYDRINATE TABLETS

Antiemetic

Original formula

• Fast acting motion sickness relief

• For children & adults

36 TABLETS (50 mg EACH)